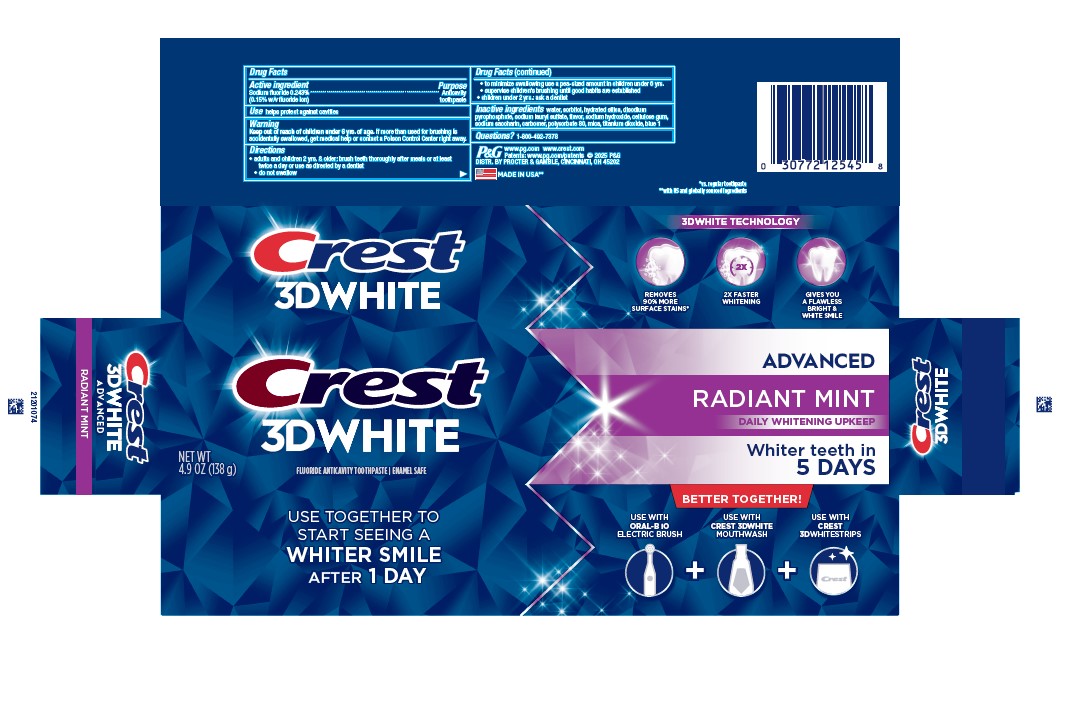 DRUG LABEL: Crest 3D White
NDC: 69423-770 | Form: PASTE, DENTIFRICE
Manufacturer: The Procter & Gamble Manufacturing Company
Category: otc | Type: HUMAN OTC DRUG LABEL
Date: 20260205

ACTIVE INGREDIENTS: SODIUM FLUORIDE 1.5 mg/1 g
INACTIVE INGREDIENTS: CARBOXYPOLYMETHYLENE; SODIUM POLYMETAPHOSPHATE; SODIUM LAURYL SULFATE; SODIUM HYDROXIDE; CARBOXYMETHYLCELLULOSE SODIUM; FD&C BLUE NO. 1; POLYSORBATE 80; SORBITOL; WATER; TITANIUM DIOXIDE; HYDRATED SILICA; SACCHARIN SODIUM; MICA

Crest 3D White Advanced Radiant Mint

Drug Facts

Active ingredient

Sodium fluoride 0.243% (0.15% w/v fluoride ion)

Purpose

Anticavity toothpaste

Use

helps protect against cavities

Warning

Keep out of reach of children under 6 yrs. of age. If more than used for brushing is accidentally swallowed, get medical help or contact a Poison Control Center right away.

Directions

- adults and children 2 yrs. & older: brush teeth thoroughly after meals or at least twice a day or use as directed by a dentist
- do not swallow
- to minimize swallowing use a pea-sized amount in children under 6
- supervise children's brushing until good habits are established
- children under 2 yrs.: ask a dentist

Inactive ingredients

water, sorbitol, hydrated silica, disodium
pyrophosphate, sodium lauryl sulfate, flavor, sodium hydroxide, cellulose gum,
sodium saccharin, carbomer, polysorbate 80, mica, titanium dioxide, blue 1

Questions?

1-800-492-7378

DISTR. BY PROCTER & GAMBLE, CINCINNATI, OH 45202

PRINCIPAL DISPLAY PANEL - 138 g Tube Carton

CREST

3D WHITE

ADVANCED

RADIANT MINT

daily whitening upkeep

Whiter Teeth in 5 DAYS

new wt 4.9 oz (138 g)

fluoride anticavity toothpaste

enamel safe